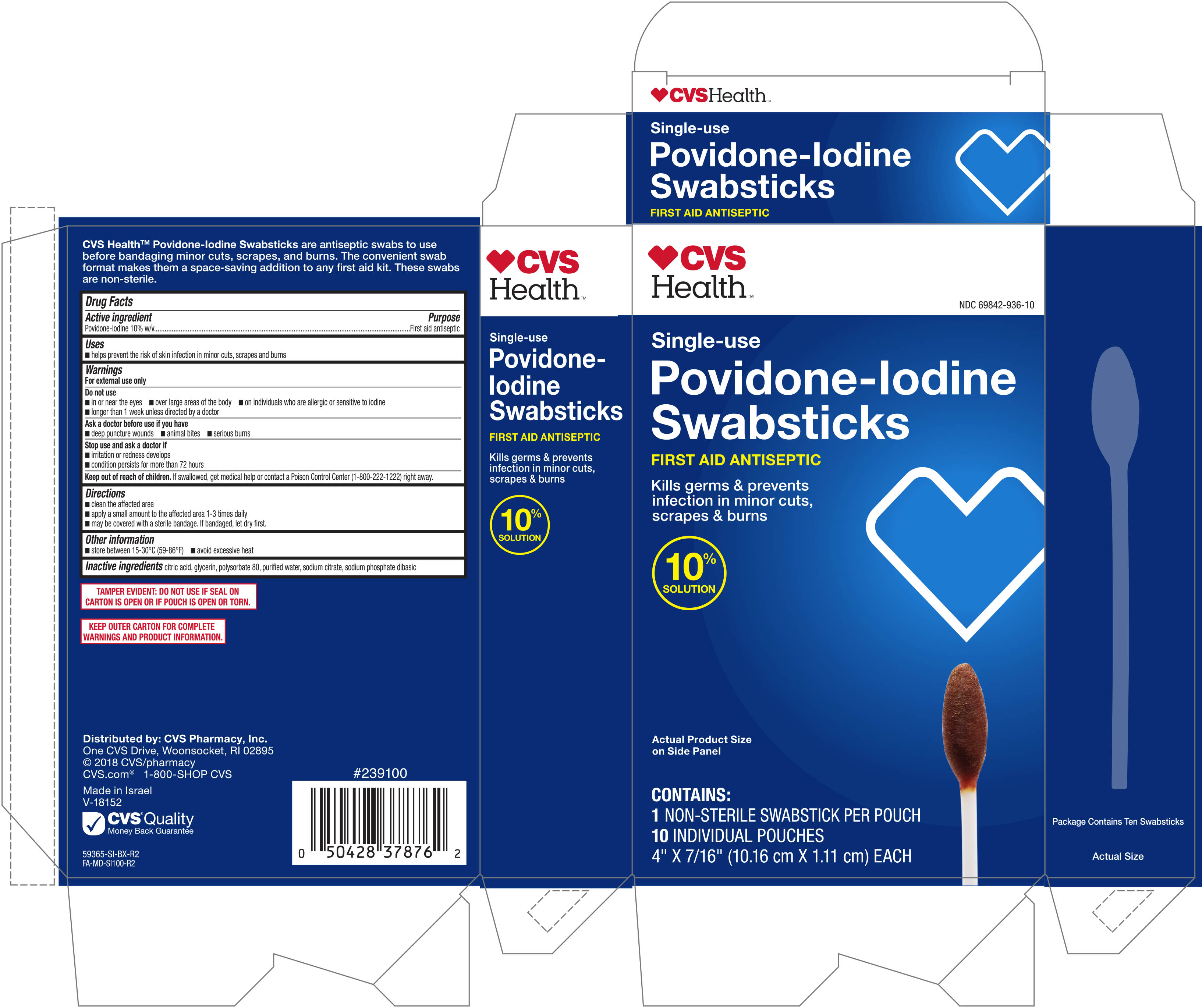 DRUG LABEL: CVS Health Povidone Iodine Swabstick
NDC: 69842-936 | Form: SWAB
Manufacturer: CVS Pharmacy Inc
Category: otc | Type: HUMAN OTC DRUG LABEL
Date: 20190312

ACTIVE INGREDIENTS: POVIDONE-IODINE 10 mg/1 mL
INACTIVE INGREDIENTS: SODIUM CITRATE; ANHYDROUS CITRIC ACID; POLYSORBATE 80; WATER; SODIUM PHOSPHATE DIBASIC DIHYDRATE; GLYCERIN

CVS Health Povidone-Iodine Swabsticks Single Use 10ct 59365 (2019)

Active ingredient Purpose

Povidone-Iodine 10% v/v................................................First aid antiseptic

Uses

- helps prevent the risk of skin infection in minor cuts, scrapes and burns

Warnings

For external use only

Do not use

- in or near the eyes
- over large areas of the body
- on individuals who are allergic or sensitive to iodine
- longer than 1 week unless directed by a doctor

Ask a doctor before use if you have

- deep puncture wounds
- animal bites
- serious burns

Stop use and ask a doctor if

- irritation or redness develops
- condition persists for more than 72 hours

Keep out of reach of children. If swallowed, get medical help or contact a Poison Control Center (1-800-222-1222) right away.

Directions

- clean the affected area
- apply a small amount to the affected area 1-3 times daily
- may be covered with a sterile bandage. If bandaged, let dry first.

Other information

- store between 15-30°C (59-86°F)
- avoid excessive heat

Inactive ingredients

citric acid, glycerin, polysorbate 80, purified water, sodium citrate, sodium phosphate dibasic

DOSAGE AND ADMINISTRATION

Distributed by:

CVS Pharmacy, Inc.

One CVS Drive

Woonsocket, RI 02895

Made in Israel